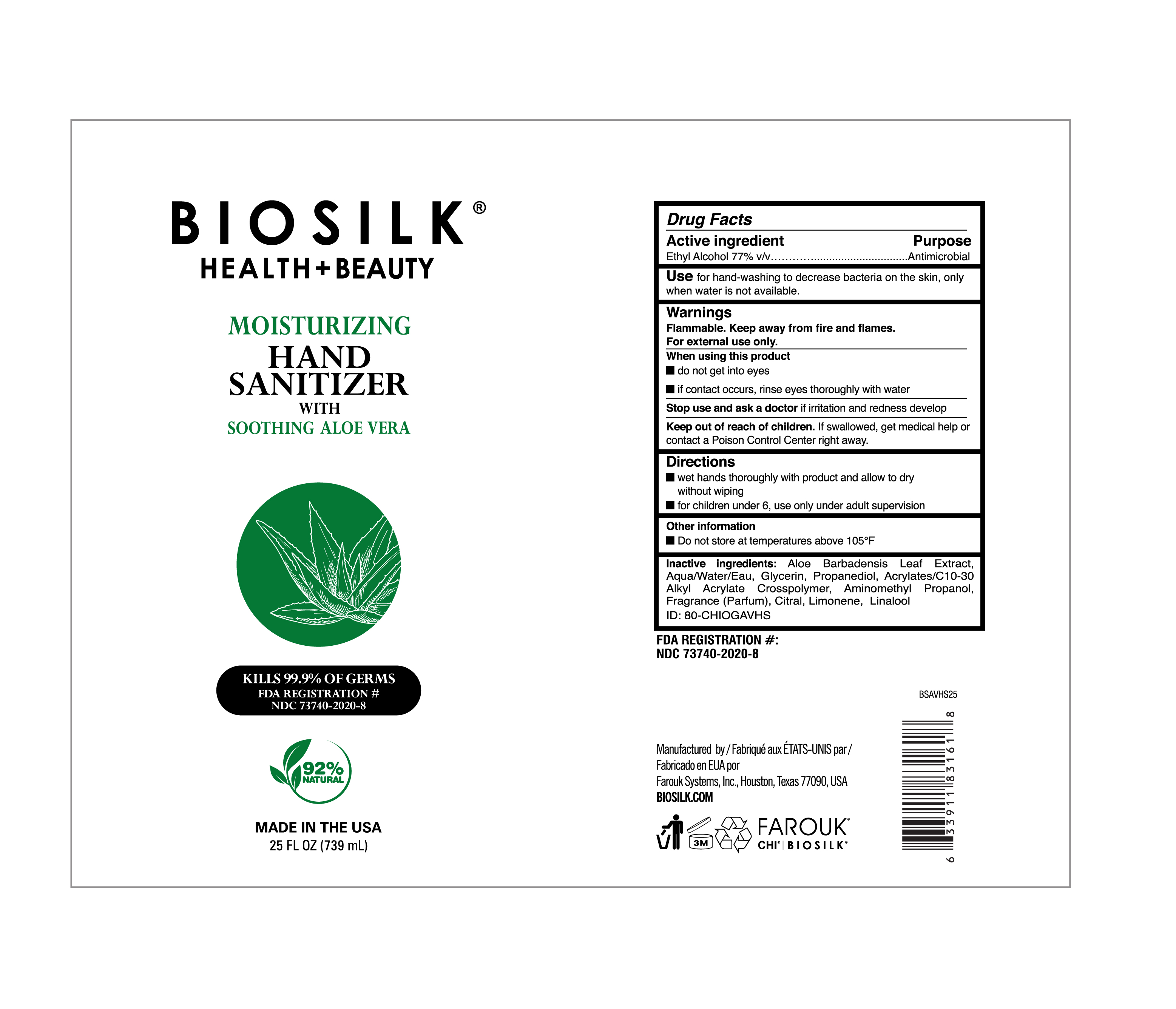 DRUG LABEL: BioSilk Hand Sanitizer
NDC: 73740-2020 | Form: GEL
Manufacturer: Farouk Systems, Inc.
Category: otc | Type: HUMAN OTC DRUG LABEL
Date: 20201124

ACTIVE INGREDIENTS: ALCOHOL 77 g/100 g
INACTIVE INGREDIENTS: LIMONENE, (+)- 0.14625 g/100 g; AMINOMETHYL PROPANEDIOL 0.095 g/100 g; (C10-C30)ALKYL METHACRYLATE ESTER 0.4 g/100 g; LINALOOL, (+)- 0.00475 g/100 g; WATER 6.255 g/100 g; GLYCERIN 2 g/100 g; ALOE VERA LEAF 28.5 g/100 g; PROPANEDIOL 2 g/100 g; CITRAL 0.0275 g/100 g; FRAGRANCE LAVENDER & CHIA F-153480 0.0715 g/100 g

Biosilk Health + Beauty Hand Sanitizer

Stop use and ask a doctor if irritation and redness develop

Directions

wet hands thoroughly with product and allow to dry without wiping.

for children under 6, use only under adult supervision.

Warnings

Flammable. Keep away from fire and flames.

For external use only.

When using this product

do not get in eyes

if contact occurrs, rinse eyes thoroughly with water.

Active Ingredient

Ethyl Alcohol 77% v/v Purpose Antimicrobial

Stop use and ask a doctor if irritation and redness develop.

Keep out of reach of children. If swallowed, get medical help or contact a Poison Control Center right away.

Use

Use for hand washing to decrease bacteria on the skin, only when water is not available.

Inactive ingredients

Inactive ingredients: Aloe Barbadensis Leaf Extract, Aqua/Water/Eau, Glycerin, Propanediol, Acrylates/C10-30 Alkyl Acrelate Crosspolymer, Aminomethyl Propanol, Fragrance (Parfum), Citral, Limonene, Linalool.

Warnings

Flammable. Keep away from fire and flames.

For external use only.

Use

Use for hand washing to decrease bacteria on the skin, only when water is not available.

Biosilk Health + Beauty

Moisturizing Hand Sanitizer

with Soothing Aloe Vera

Kills 99.9% of germs

FDA REgistration # NDC 73740-2020-8

92% Natural

Made in the USA

25 FL OZ (739 mL)